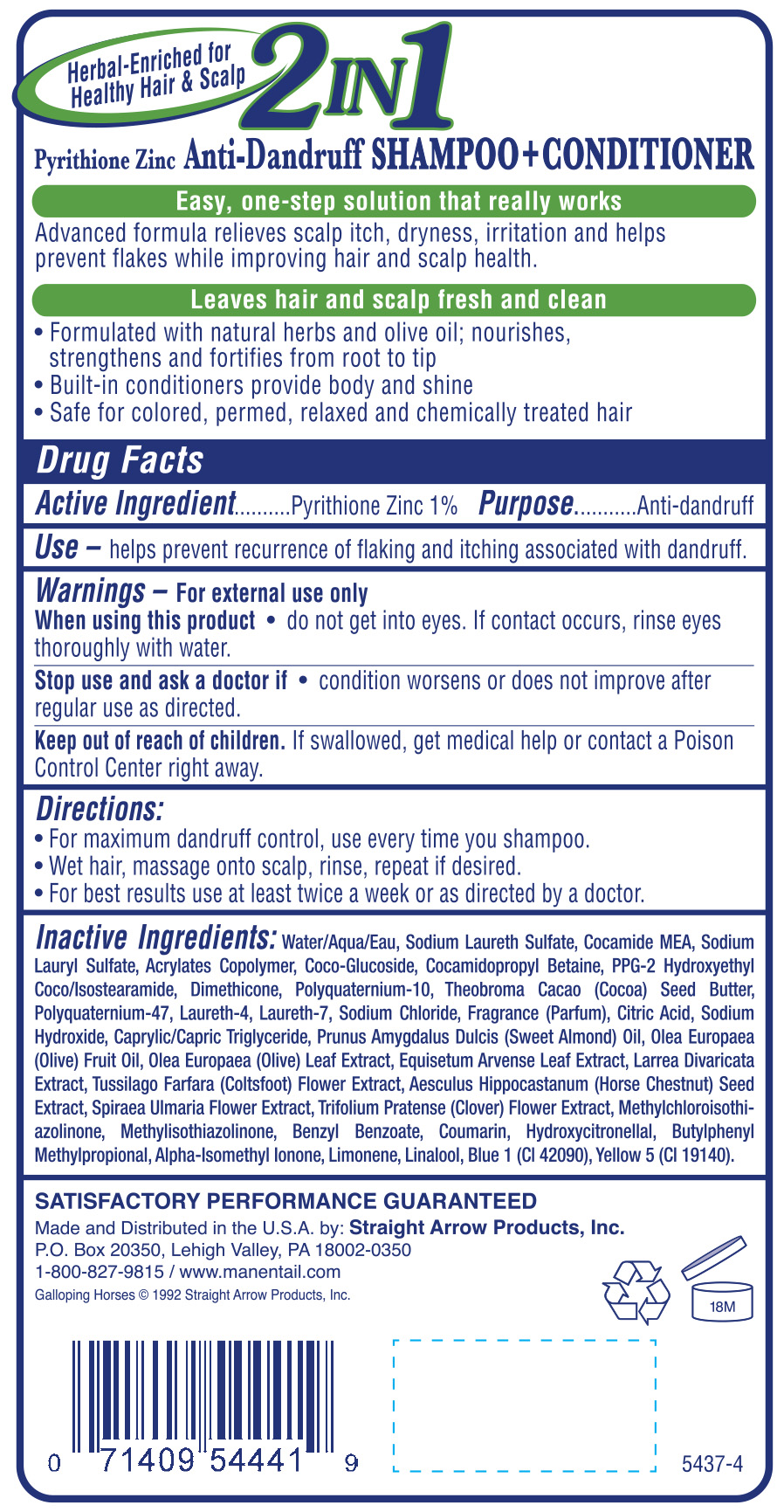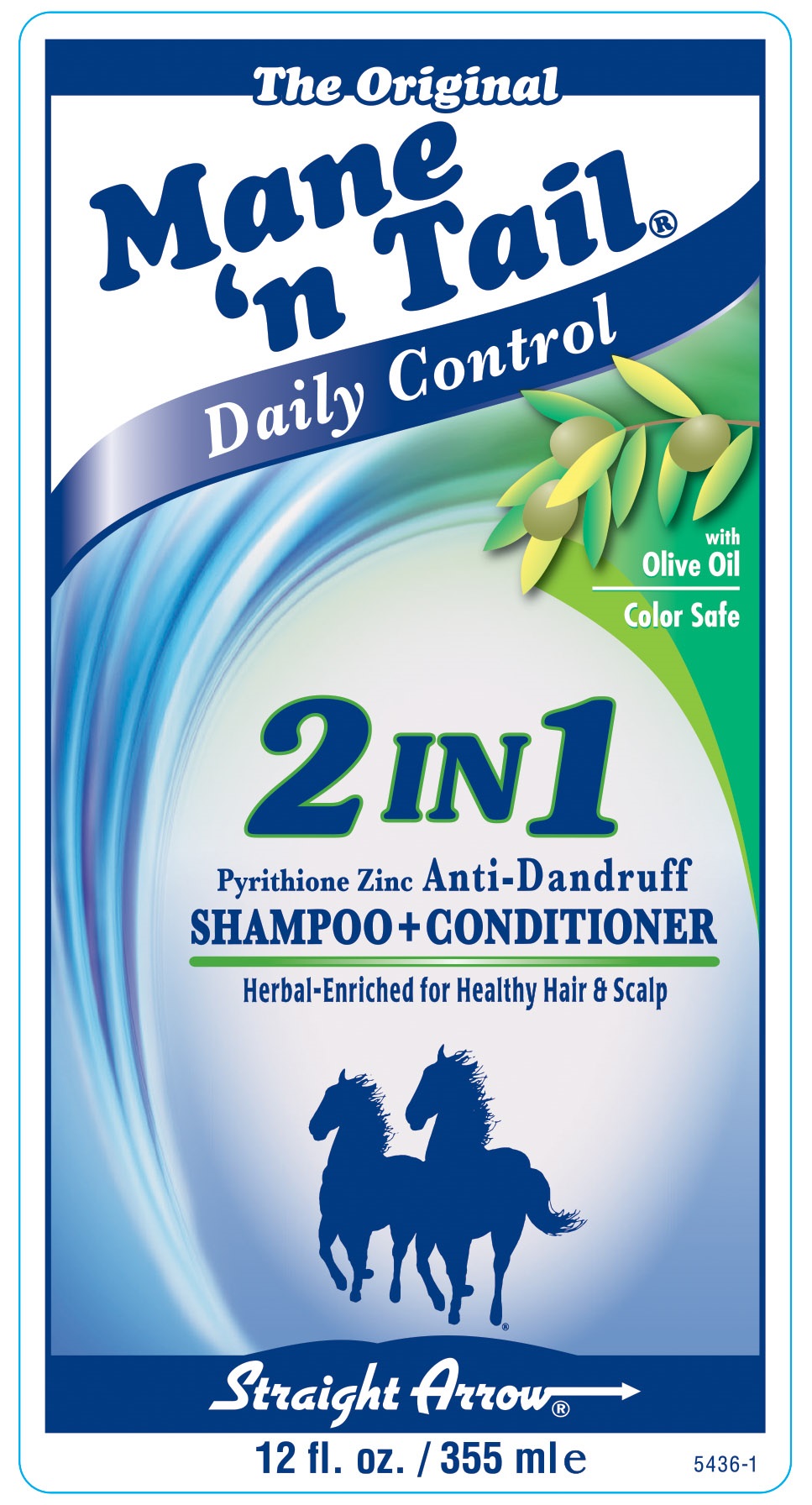 DRUG LABEL: The Original Mane n Tail Daily Control 2 in 1 Anti Dandruff
NDC: 62001-0330 | Form: SHAMPOO
Manufacturer: Straight Arrow Products Inc
Category: otc | Type: HUMAN OTC DRUG LABEL
Date: 20250702

ACTIVE INGREDIENTS: PYRITHIONE ZINC .01 g/.01 g
INACTIVE INGREDIENTS: WATER; SODIUM LAURETH SULFATE; COCO MONOETHANOLAMIDE; SODIUM LAURYL SULFATE; BUTYL ACRYLATE/METHYL METHACRYLATE/METHACRYLIC ACID COPOLYMER (18000 MW); COCO GLUCOSIDE; COCAMIDOPROPYL BETAINE; PPG-2 HYDROXYETHYL COCO/ISOSTEARAMIDE; DIMETHICONE; POLYQUATERNIUM-10 (400 CPS AT 2%); COCOA BUTTER; POLYQUATERNIUM-47 (METHACRYLAMIDOPROPYLTRIMETHYLAMMONIUM CHLORIDE-CO-METHYL ACRYLATE-CO-ACRYLIC ACID 45:10:45; 1200000 MW); LAURETH-4; LAURETH-7; SODIUM CHLORIDE; ANHYDROUS CITRIC ACID; SODIUM HYDROXIDE; MEDIUM-CHAIN TRIGLYCERIDES; ALMOND OIL; OLIVE OIL; OLEA EUROPAEA LEAF; EQUISETUM ARVENSE BRANCH; LARREA DIVARICATA LEAF; TUSSILAGO FARFARA FLOWER; HORSE CHESTNUT; FILIPENDULA ULMARIA FLOWER; TRIFOLIUM PRATENSE FLOWER; METHYLCHLOROISOTHIAZOLINONE; METHYLISOTHIAZOLINONE; BENZYL BENZOATE; COUMARIN; HYDROXYCITRONELLAL; BUTYLPHENYL METHYLPROPIONAL; ISOMETHYL-.ALPHA.-IONONE; LIMONENE, (+)-; LINALOOL, (+/-)-; FD&C BLUE NO. 1; FD&C YELLOW NO. 5

The Original Mane n Tail Daily Control 2 in 1 Anti Dandruff

Active Ingredient Pyrithione Zinc 1%

Purpose Anti-dandruff

INDICATIONS AND USAGE

Use -helps prevent recurrence of flaking and itchng associated with dandruff.

Warnings -For external use only

when using this product • do not get into eyes. If contact occurs, rinse eyes thoroughly with water.

Stop use and ask a doctor if condition worsens or does not improve after regular use as directed.

Keep out of reach of children. If swallowed, get medical help or contact a Poison Control Center right away.

Directions:

- For maximum dandruff control, use every time you shampoo.
- Wet hair, massage onto scalp, rinse, repeat if desired.
- For best results, use at least twice a week or as directed by a doctor.

INACTIVE INGREDIENT

Inactive Ingredients: Water/Aqua/Eau(Water), Sodium Laureth Sulfate, Cocamide MEA, Sodium Lauryl Sulfate, Acrylates Copolymer, Coco Glucoside, Cocamidopropyl Betaine, PPG-2 Hydroxyethyl Coco/Isostearamide, Dimethicone, Polyquaternium-10, Theobroma Cocao (cocoa) Seed Butter, Polyquaternium-47, Laureth-4, Laureth-7, Sodium Chloride, Fragrance (Parfum), Citric Acid, Sodium Hydroxide, Caprylic/Capric Triglyceride, Prunus Amagdalus Dulcis (Sweet Almond) Seed Oil, Olea Europaea (Olive) Fruit Oil, Olea Europaea (Olive) Leaf Extract, Equisetum Arvense (Horsetail) Leaf Extract, Larrea Divaricata (Chaparral) Extract, Tussilago Farfara (Coltsfoot) Flower Extract, Aesculus Hippocastanum (Horse Chestnut) Seed Extract, Spiraea Ulmaria (Meadowsweet) Flower Extract, Trifolium Pratense (Clover) Flower Extract, Methylchloroisothiazolinone, Methylisothiazolinone, Benzyl Benzoate, Coumarin, Hydroxycitronellal, Butylphenyl Methylpropional, Alpha-isomethyl ionone, Limonene, Linalool, Blue 1 (CI 42090), Yellow 5 (CI 19140).